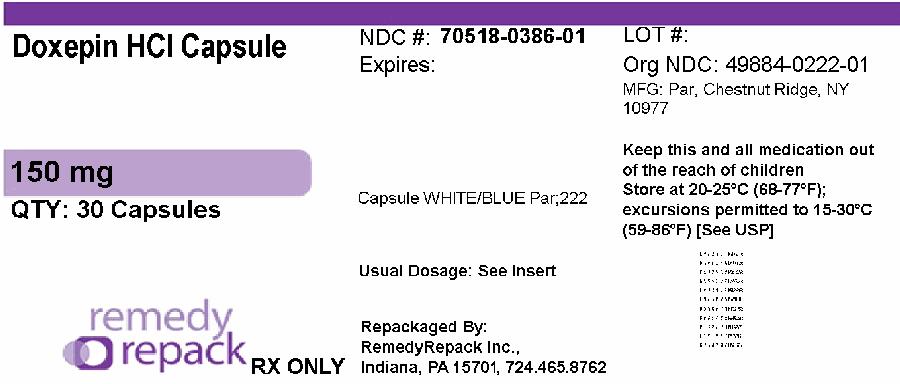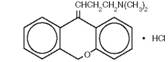 DRUG LABEL: Doxepin Hydrochloride
NDC: 70518-0386 | Form: CAPSULE
Manufacturer: REMEDYREPACK INC.
Category: prescription | Type: HUMAN PRESCRIPTION DRUG LABEL
Date: 20260105

ACTIVE INGREDIENTS: DOXEPIN HYDROCHLORIDE 150 mg/1 1
INACTIVE INGREDIENTS: D&C YELLOW NO. 10; STARCH, CORN; FD&C BLUE NO. 1; GELATIN; MAGNESIUM STEARATE; SODIUM LAURYL SULFATE; TITANIUM DIOXIDE

DOXEPIN HYDROCHLORIDE CAPSULES USP

Suicidality and Antidepressant Drugs

Antidepressants increased the risk compared to placebo of suicidal thinking and behavior (suicidality) in children, adolescents, and young adults in short-term studies of major depressive disorder (MDD) and other psychiatric disorders. Anyone considering the use of doxepin hydrochloride or any other antidepressant in a child, adolescent, or young adult must balance this risk with the clinical need. Short-term studies did not show an increase in the risk of suicidality with antidepressants compared to placebo in adults beyond age 24; there was a reduction in risk with antidepressants compared to placebo in adults aged 65 and older. Depression and certain other psychiatric disorders are themselves associated with increases in the risk of suicide. Patients of all ages who are started on antidepressant therapy should be monitored appropriately and observed closely for clinical worsening, suicidality, or unusual changes in behavior. Families and caregivers should be advised of the need for close observation and communication with the prescriber. Doxepin hydrochloride is not approved for use in pediatric patients. (See WARNINGS: Clinical Worsening and Suicide Risk, PRECAUTIONS: Information for Patients, and PRECAUTIONS: Pediatric Use).

DESCRIPTION

Doxepin hydrochloride is one of a class of psychotherapeutic agents known as dibenzoxepin tricyclic compounds. The molecular formula of the compound is C19H21NO•HCl having a molecular weight of 315.84. It is a white crystalline solid readily soluble in water, lower alcohols and chloroform. Its structural formula is:

C19H21NO●HCl | MW: 315.84

Chemically,Doxepin HCl is a dibenzoxepin derivative and is the first of a family of tricyclic psychotherapeutic agents. Specifically, it is an isomeric mixture of: 1-Propanamine, 3-dibenz[b,e]oxepin-11(6 H)ylidene- N,N-dimethyl-hydrochloride. Each doxepin hydrochloride capsule is equivalent to 10 mg, 25 mg, 50 mg, 75 mg, 100 mg, and 150 mg of doxepin for oral administration.

Each capsule contains the following inactive ingredients: corn starch, D&C Yellow #10, FD&C Blue #1, FD&C Blue #2, FD&C Red #40, gelatin, magnesium stearate, pharmaceutical glaze, sodium lauryl sulfate, synthetic black iron oxide, titanium dioxide and other ingredients. In addition, the 10 mg capsule contains FD&C Yellow #6; the 25 mg and 50 mg capsules contain FD&C Yellow #6 and propylene glycol; the 75 mg capsule contains FD&C Green #3 and propylene glycol, and the 100 mg capsule contains FD&C Green #3.

CLINICAL PHARMACOLOGY

The mechanism of action of doxepin HCl is not definitely known. It is not a central nervous system stimulant nor a monoamine oxidase inhibitor. The current hypothesis is that the clinical effects are due, at least in part, to influences on the adrenergic activity at the synapses so that deactivation of norepinephrine by reuptake into the nerve terminals is prevented. Animal studies suggest that doxepin HCl does not appreciably antagonize the antihypertensive action of guanethidine. In animal studies anticholinergic, anti-serotonin and antihistamine effects on smooth muscle have been demonstrated. At higher than usual clinical doses, norepinephrine response was potentiated in animals. This effect was not demonstrated in humans.

At clinical dosages up to 150 mg per day, doxepin HCl can be given to man concomitantly with guanethidine and related compounds without blocking the antihypertensive effect. At dosages above 150 mg per day blocking of the antihypertensive effect of these compounds has been reported.

Doxepin HCl is virtually devoid of euphoria as a side effect. Characteristic of this type of compound, doxepin HCl has not been demonstrated to produce the physical tolerance or psychological dependence associated with addictive compounds.

INDICATIONS AND USAGE

Doxepin HCl is recommended for the treatment of:

1.Psychoneurotic patients with depression and/or anxiety.

2.Depression and/or anxiety associated with alcoholism (not to be taken concomitantly with alcohol).

3.Depression and/or anxiety associated with organic disease (the possibility of drug interaction should be considered if the patient is receiving other drugs concomitantly).

4.Psychotic depressive disorders with associated anxiety including involutional depression and manic-depressive disorders.

The target symptoms of psychoneurosis that respond particularly well to doxepin HCl include anxiety, tension, depression, somatic symptoms and concerns, sleep disturbances, guilt, lack of energy, fear, apprehension and worry.

Clinical experience has shown that doxepin HCl is safe and well tolerated even in the elderly patient. Owing to lack of clinical experience in the pediatric population, doxepin HCl is not recommended for use in children under 12 years of age.

CONTRAINDICATIONS

Doxepin HCl is contraindicated in individuals who have shown hypersensitivity to the drug. Possibility of cross sensitivity with other dibenzoxepines should be kept in mind.

Doxepin HCl is contraindicated in patients with glaucoma or a tendency to urinary retention. These disorders should be ruled out, particularly in older patients.

WARNINGS

Clinical Worsening and Suicide Risk

Patients with major depressive disorder (MDD), both adult and pediatric, may experience worsening of their depression and/or the emergence of suicidal ideation and behavior (suicidality) or unusual changes in behavior, whether or not they are taking antidepressant medications, and this risk may persist until significant remission occurs. Suicide is a known risk of depression and certain other psychiatric disorders, and these disorders themselves are the strongest predictors of suicide. There has been a long-standing concern, however, that antidepressants may have a role in inducing worsening of depression and the emergence of suicidality in certain patients during the early phases of treatment. Pooled analyses of short-term placebo-controlled trials of antidepressant drugs (SSRIs and others) showed that these drugs increase the risk of suicidal thinking and behavior (suicidality) in children, adolescents, and young adults (ages 18 to 24) with major depressive disorder (MDD) and other psychiatric disorders. Short-term studies did not show an increase in the risk of suicidality with antidepressants compared to placebo in adults beyond age 24; there was a reduction with antidepressants compared to placebo in adults aged 65 and older.

The pooled analyses of placebo-controlled trials in children and adolescents with MDD, obsessive compulsive disorder (OCD), or other psychiatric disorders included a total of 24 short-term trials of 9 antidepressant drugs in over 4400 patients. The pooled analyses of placebo-controlled trials in adults with MDD or other psychiatric disorders included a total of 295 short-term trials (median duration of 2 months) of 11 antidepressant drugs in over 77,000 patients. There was considerable variation in risk of suicidality among drugs, but a tendency toward an increase in the younger patients for almost all drugs studied. There were differences in absolute risk of suicidality across the different indications, with the highest incidence in MDD. The risk differences (drug vs placebo), however, were relatively stable within age strata and across indications. These risk differences (drug-placebo difference in the number of cases of suicidality per 1000 patients treated) are provided in Table 1.

Table 1
Age Range | Drug-Placebo Difference in Number of Cases of Suicidality per 1000 Patients Treated
 | Increases Compared to Placebo
< 18 | 14 additional cases
18 to 24 | 5 additional cases
 | Decreases Compared to Placebo
25 to 64 | 1 fewer case
≥ 65 | 6 fewer cases

No suicides occurred in any of the pediatric trials. There were suicides in the adult trials, but the number was not sufficient to reach any conclusion about drug effect on suicide.

It is unknown whether the suicidality risk extends to longer-term use, i.e., beyond several months. However, there is substantial evidence from placebo-controlled maintenance trials in adults with depression that the use of antidepressants can delay the recurrence of depression.

All patients being treated with antidepressants for any indication should be monitored appropriately and observed closely for clinical worsening, suicidality, and unusual changes in behavior, especially during the initial few months of a course of drug therapy, or at times of dose changes, either increases or decreases.

The following symptoms, anxiety, agitation, panic attacks, insomnia, irritability, hostility, aggressiveness, impulsivity, akathisia (psychomotor restlessness), hypomania, and mania, have been reported in adult and pediatric patients being treated with antidepressants for major depressive disorder as well as for other indications, both psychiatric and nonpsychiatric. Although a causal link between the emergence of such symptoms and either the worsening of depression and/or the emergence of suicidal impulses has not been established, there is concern that such symptoms may represent precursors to emerging suicidality.

Consideration should be given to changing the therapeutic regimen, including possibly discontinuing the medication, in patients whose depression is persistently worse, or who are experiencing emergent suicidality or symptoms that might be precursors to worsening depression or suicidality, especially if these symptoms are severe, abrupt in onset, or were not part of the patient's presenting symptoms.

Families and caregivers of patients being treated with antidepressants for major depressive disorder or other indications, both psychiatric and nonpsychiatric, should be alerted about the need to monitor patients for the emergence of agitation, irritability, unusual changes in behavior, and the other symptoms described above, as well as the emergence of suicidality, and to report such symptoms immediately to health care providers. Such monitoring should include daily observation by families and caregivers.Prescriptions for doxepin hydrochloride should be written for the smallest quantity of tablets consistent with good patient management, in order to reduce the risk of overdose.

Screening Patients for Bipolar Disorder:A major depressive episode may be the initial presentation of bipolar disorder. It is generally believed (though not established in controlled trials) that treating such an episode with an antidepressant alone may increase the likelihood of precipitation of a mixed/manic episode in patients at risk for bipolar disorder. Whether any of the symptoms described above represent such a conversion is unknown. However, prior to initiating treatment with an antidepressant, patients with depressive symptoms should be adequately screened to determine if they are at risk for bipolar disorder; such screening should include a detailed psychiatric history, including a family history of suicide, bipolar disorder, and depression. It should be noted that doxepin hydrochloride is not approved for use in treating bipolar depression.

Angle-Closure Glaucoma

The pupillary dilation that occurs following use of many antidepressant drugs including Doxepin Hydrochloride Capsules may trigger an angle closure attack in a patient with anatomically narrow angles who does not have a patent iridectomy.

Geriatric Use

The use of doxepin HCl on a once-a-day dosage regimen in geriatric patients should be adjusted carefully based on the patient’s condition (see PRECAUTIONS-Geriatric Use).

Pregnancy

Reproduction studies have been performed in rats, rabbits, monkeys and dogs and there was no evidence of harm to the animal fetus. The relevance to humans is not known. Since there is no experience in pregnant women who have received this drug, safety in pregnancy has not been established. There has been a report of apnea and drowsiness occurring in a nursing infant whose mother was taking doxepin hydrochloride.

Pediatric Use

The use of doxepin HCl in children under 12 years of age is not recommended because safe conditions for its use have not been established.

PRECAUTIONS

Information for Patients

Prescribers or other health professionals should inform patients, their families, and their caregivers about the benefits and risks associated with treatment with doxepin hydrochloride and should counsel them in its appropriate use. A patient Medication Guide about “Antidepressant Medicines, Depression and other Serious Mental Illness, and Suicidal Thoughts or Actions” is available for doxepin hydrochloride. The prescriber or health professional should instruct patients, their families, and their caregivers to read the Medication Guide and should assist them in understanding its contents. Patients should be given the opportunity to discuss the contents of the Medication Guide and to obtain answers to any questions they may have. The complete text of the Medication Guide is reprinted at the end of this document.

Patients should be advised of the following issues and asked to alert their prescriber if these occur while taking doxepin hydrochloride.

Patients should be advised that taking Doxepin Hydrochloride Capsules can cause mild pupillary dilation, which in susceptible individuals, can lead to an episode of angle-closure glaucoma. Pre-existing glaucoma is almost always open-angle glaucoma because angle-closure glaucoma, when diagnosed, can be treated definitively with iridectomy. Open-angle glaucoma is not a risk factor for angle closure glaucoma. Patients may wish to be examined to determine whether they are susceptible to angle closure, and have a prophylactic procedure (e.g., iridectomy), if they are susceptible.

Clinical Worsening and Suicide Risk:

Patients, their families, and their caregivers should be encouraged to be alert to the emergence of anxiety, agitation, panic attacks, insomnia, irritability, hostility, aggressiveness, impulsivity, akathisia (psychomotor restlessness), hypomania, mania, other unusual changes in behavior, worsening of depression, and suicidal ideation, especially early during antidepressant treatment and when the dose is adjusted up or down. Families and caregivers of patients should be advised to look for the emergence of such symptoms on a day-to-day basis, since changes may be abrupt. Such symptoms should be reported to the patient's prescriber or health professional, especially if they are severe, abrupt in onset, or were not part of the patient's presenting symptoms. Symptoms such as these may be associated with an increased risk for suicidal thinking and behavior and indicate a need for very close monitoring and possibly changes in the medication.

Repackaged By / Distributed By: RemedyRepack Inc.

625 Kolter Drive, Indiana, PA 15701

(724) 465-8762

Drug Interactions

Drugs Metabolized by P450 2D6: The biochemical activity of the drug metabolizing isozyme cytochrome P450 2D6 (debrisoquin hydroxylase) is reduced in a subset of the Caucasian population (about 7 to 10% of Caucasians are so-called “poor metabolizers”); reliable estimates of the prevalence of reduced P450 2D6 isozyme activity among Asian, African and other populations are not yet available. Poor metabolizers have higher than expected plasma concentrations of tricyclic antidepressants (TCAs) when given usual doses. Depending on the fraction of drug metabolized by P450 2D6, the increase in plasma concentration may be small, or quite large (8-fold increase in plasma AUC of the TCA).

In addition, certain drugs inhibit the activity of this isozyme and make normal metabolizers resemble poor metabolizers. An individual who is stable on a given dose of TCA may become abruptly toxic when given one of these inhibiting drugs as concomitant therapy. The drugs that inhibit cytochrome P450 2D6 include some that are not metabolized by the enzyme (quinidine; cimetidine) and many that are substrates for P450 2D6 (many other antidepressants, phenothiazines, and the Type 1C antiarrhythmics propafenone and flecainide). While all the selective serotonin reuptake inhibitors (SSRIs), e.g., citalopram, escitalopram, fluoxetine, sertraline, and paroxetine, inhibit P450 2D6, they may vary in the extent of inhibition. The extent to which SSRI-TCA interactions may pose clinical problems will depend on the degree of inhibition and the pharmacokinetics of the SSRI involved. Nevertheless, caution is indicated in the co-administration of TCAs with any of the SSRIs and also in switching from one class to the other. Of particular importance, sufficient time must elapse before initiating TCA treatment in a patient being withdrawn from fluoxetine, given the long half-life of the parent and active metabolite (at least 5 weeks may be necessary).

Concomitant use of tricyclic antidepressants with drugs that can inhibit cytochrome P450 2D6 may require lower doses than usually prescribed for either the tricyclic antidepressant or the other drug. Furthermore, whenever one of these other drugs is withdrawn from co-therapy, an increased dose of tricyclic antidepressant may be required. It is desirable to monitor TCA plasma levels whenever a TCA is going to be co-administered with another drug known to be an inhibitor of P450 2D6.

Doxepin is primarily metabolized by CYP2D6 (with CYP1A2 & CYP3A4 as minor pathways). Inhibitors or substrates of CYP2D6 (i.e., quinidine, selective serotonin reuptake inhibitors [SSRIs]) may increase the plasma concentration of doxepin when administered concomitantly. The extent of interaction depends on the variability of effect on CYP2D6. The clinical significance of this interaction with doxepin has not been systematically evaluated.

MAO Inhibitors

Serious side effects and even death have been reported following the concomitant use of certain drugs with MAO inhibitors. Therefore, MAO inhibitors should be discontinued at least two weeks prior to the cautious initiation of therapy with doxepin HCl. The exact length of time may vary and is dependent upon the particular MAO inhibitor being used, the length of time it has been administered, and the dosage involved.

Cimetidine

Cimetidine has been reported to produce clinically significant fluctuations in steady-state serum concentrations of various tricyclic antidepressants. Serious anticholinergic symptoms (i.e., severe dry mouth, urinary retention and blurred vision) have been associated with elevations in the serum levels of tricyclic antidepressants when cimetidine therapy is initiated. Additionally, higher than expected tricyclic antidepressant levels have been observed when they are begun in patients already taking cimetidine. In patients who have been reported to be well controlled on tricyclic antidepressants receiving concurrent cimetidine therapy, discontinuation of cimetidine has been reported to decrease established steady-state serum tricyclic antidepressant levels and compromise their therapeutic effects.

Alcohol

It should be borne in mind that alcohol ingestion may increase the danger inherent in any intentional or unintentional doxepin HCl overdosage. This is especially important in patients who may use alcohol excessively.

Tolazamide

A case of severe hypoglycemia has been reported in a type II diabetic patient maintained on tolazamide (1 gm/day) 11 days after the addition of doxepin (75 mg/day).

Drowsiness

Since drowsiness may occur with the use of this drug, patients should be warned of the possibility and cautioned against driving a car or operating dangerous machinery while taking the drug. Patients should also be cautioned that their response to alcohol may be potentiated.

Sedating drugs may cause confusion and over sedation in the elderly; elderly patients generally should be started on low doses of doxepin HCl and observed closely (see PRECAUTIONS-Geriatric Use).

Suicide

Since suicide is an inherent risk in any depressed patient and may remain so until significant improvement has occurred, patients should be closely supervised during the early course of therapy. Prescriptions should be written for the smallest feasible amount.

Psychosis

Should increased symptoms of psychosis or shift to manic symptomatology occur, it may be necessary to reduce dosage or add a major tranquilizer dosage regimen.

Pediatric Use:Safety and effectiveness in the pediatric population have not been established (see BOX WARNINGand WARNINGS – Clinical Worsening and Suicide Risk). Anyone considering the use of doxepin HCl in a child or adolescent must balance the potential risks with the clinical need.

Geriatric Use

A determination has not been made whether controlled clinical studies of doxepin HCl included sufficient numbers of subjects aged 65 and over to define a difference in response from younger subjects. Other reported clinical experience has not identified differences in responses between the elderly and younger patients. In general, dose selection for an elderly patient should be cautious, usually starting at the low end of the dosing range, reflecting the greater frequency of decreased hepatic, renal or cardiac function, and of concomitant disease or other drug therapy.

The extent of renal excretion of doxepin HCl has not been determined. Because elderly patients are more likely to have decreased renal function, care should be taken in dose selections.

Sedating drugs may cause confusion and over sedation in the elderly; elderly patients generally should be started on low doses of doxepin HCl and observed closely. (See WARNINGS.)

ADVERSE REACTIONS

NOTE:

Some of the adverse reactions noted below have not been specifically reported with doxepin HCl use. However, due to the close pharmacological similarities among the tricyclics, the reactions should be considered when prescribing doxepin HCl.

Anticholinergic Effects:

Dry mouth, blurred vision, constipation, and urinary retention have been reported. If they do not subside with continued therapy, or become severe, it may be necessary to reduce the dosage.

Central Nervous System Effects:

Drowsiness is the most commonly noticed side effect. This tends to disappear as therapy is continued. Other infrequently reported CNS side effects are confusion, disorientation, hallucinations, numbness, paresthesia, ataxia, extrapyramidal symptoms, seizures, tardive dyskinesia and tremor.

Cardiovascular:

Cardiovascular effects including hypotension, hypertension, and tachycardia have been reported occasionally.

Allergic:

Skin rash, edema, photosensitization, and pruritus have occasionally occurred.

Hematologic:

Eosinophilia has been reported in a few patients. There have been occasional reports of bone marrow depression manifesting as agranulocytosis, leukopenia, thrombocytopenia, and purpura.

Gastrointestinal:

Nausea, vomiting, indigestion, taste disturbances, diarrhea, anorexia, and aphthous stomatitis have been reported. (See Anticholinergic Effects.)

Endocrine:

Raised or lowered libido, testicular swelling, gynecomastia in males, enlargement of breasts and galactorrhea in the female, raising or lowering of blood sugar levels and syndrome of inappropriate antidiuretic hormone secretion have been reported with tricyclic administration.

Other:

Dizziness, tinnitus, weight gain, sweating, chills, fatigue, weakness, flushing, jaundice, alopecia, headache, exacerbation of asthma, and hyperpyrexia (in association with chlorpromazine) have been occasionally observed as adverse effects.

Withdrawal Symptoms:

The possibility of development of withdrawal symptoms upon abrupt cessation of treatment after prolonged doxepin HCl administration should be borne in mind. These are not indicative of addiction and gradual withdrawal of medication should not cause these symptoms.

OVERDOSAGE

Deaths may occur from overdosage with this class of drugs. Multiple drug ingestion (including alcohol) is common in deliberate tricyclic antidepressant overdose. As the management is complex and changing, it is recommended that the physician contact a poison control center for current information on treatment. Signs and symptoms of toxicity develop rapidly after tricyclic antidepressant overdose; therefore, hospital monitoring is required as soon as possible.

Manifestations:

Critical manifestations of overdose include: cardiac dysrhythmias, severe hypotension, convulsions, and CNS depression, including coma. Changes in the electrocardiogram, particularly in QRS axis or width, are clinically significant indicators of tricyclic antidepressant toxicity.

Other signs of overdose may include: confusion, disturbed concentration, transient visual hallucinations, dilated pupils, agitation, hyperactive reflexes, stupor, drowsiness, muscle rigidity, vomiting, hypothermia, hyperpyrexia, or any of the symptoms listed under ADVERSE REACTIONS.

Deaths have been reported involving overdoses of doxepin.

General Recommendations:

General

Obtain an ECG and immediately initiate cardiac monitoring. Protect the patient’s airway, establish an intravenous line and initiate gastric decontamination. A minimum of six hours of observation with cardiac monitoring and observation for signs of CNS or respiratory depression, hypotension, cardiac dysrhythmias and/or conduction blocks and seizures is strongly advised. If signs of toxicity occur at any time during this period, extended monitoring is recommended. There are case reports of patients succumbing to fatal dysrhythmias late after overdose; these patients had clinical evidence of significant poisoning prior to death and most received inadequate gastrointestinal decontamination. Monitoring of plasma drug levels should not guide management of the patient.

Gastrointestinal Decontamination

All patients suspected of tricyclic antidepressant overdose should receive gastrointestinal decontamination. This should include large volume gastric lavage followed by activated charcoal. If consciousness is impaired, the airway should be secured prior to lavage. Emesis is contraindicated.

Cardiovascular

A maximal limb-lead QRS duration of ≥ 0.10 seconds may be the best indication of the severity of the overdose. Intravenous sodium bicarbonate should be used to maintain the serum pH in the range of 7.45 to 7.55. If the pH response is inadequate, hyperventilation may also be used. Concomitant use of hyperventilation and sodium bicarbonate should be done with extreme caution, with frequent pH monitoring. A pH > 7.60 or a pCO2< 20mm Hg is undesirable. Dysrhythmias unresponsive to sodium bicarbonate therapy/hyperventilation may respond to lidocaine, bretylium or phenytoin. Type 1A and 1C antiarrhythmics are generally contraindicated (e.g., quinidine, disopyramide, and procainamide).

In rare instances, hemoperfusion may be beneficial in acute refractory cardiovascular instability in patients with acute toxicity. However, hemodialysis, peritoneal dialysis, exchange transfusions, and forced diuresis generally have been reported as ineffective in tricyclic antidepressant poisoning.

CNS

In patients with CNS depression, early intubation is advised because of the potential for abrupt deterioration. Seizures should be controlled with benzodiazepines, or if these are ineffective, other anticonvulsants (e.g., phenobarbital and phenytoin). Physostigmine is not recommended except to treat life-threatening symptoms that have been unresponsive to other therapies and only in consultation with a poison control center.

Psychiatric Follow-up

Since overdosage is often deliberate, patients may attempt suicide by other means during the recovery phase. Psychiatric referral may be appropriate.

Pediatric Management

The principles of management of child and adult overdosages are similar. It is strongly recommended that the physician contact the local poison control center for specific pediatric treatment.

DOSAGE AND ADMINISTRATION

For most patients with illness of mild to moderate severity, a starting daily dose of 75 mg is recommended. Dosage may subsequently be increased or decreased at appropriate intervals and according to individual response. The usual optimum dose range is 75 mg/day to 150 mg/day.

In more severely ill patients higher doses may be required with subsequent gradual increase to 300 mg/day if necessary. Additional therapeutic effect is rarely to be obtained by exceeding a dose of 300 mg/day.

In patients with very mild symptomatology or emotional symptoms accompanying organic disease, lower doses may suffice. Some of these patients have been controlled on doses as low as 25 to 50 mg/day.

The total daily dosage of doxepin HCl may be given on a divided or once-a-day dosage schedule. If the once-a-day schedule is employed, the maximum recommended dose is 150 mg/day. This dose may be given at bedtime. The 150 mg capsule strength is intended for maintenance therapy only and is not recommended for initiation of treatment.

Anti-anxiety effect is apparent before the antidepressant effect. Optimal antidepressant effect may not be evident for two to three weeks.

HOW SUPPLIED

Doxepin HCl capsules USP, equivalent to 150 mg of doxepin are hard gelatin capsules with white opaque body and blue opaque cap, imprinted “Par 222” on both body and cap. They are supplied in

NDC: 70518-0386-00

NDC: 70518-0386-01

PACKAGING: 30 in 1 BLISTER PACK

PACKAGING: 30 in 1 BLISTER PACK

Store at 20°to 25°C (68°-77°F) [see USP Controlled Room Temperature].

Repackaged and Distributed By:

Remedy Repack, Inc.

625 Kolter Dr. Suite #4 Indiana, PA 1-724-465-8762

Medication Guide

Doxepin Hydrochloride

(dokˊsĕ-pin hī-drō-klōrˊīd)

Capsules USP

Antidepressant Medicines, Depression and other Serious Mental Illnesses, and Suicidal Thoughts or Actions

Read the Medication Guide that comes with you or your family member’s antidepressant medicine. This Medication Guide is only about the risk of suicidal thoughts and actions with antidepressant medicines. Talk to your, or your family member’s, healthcare provider about:

- all risks and benefits of treatment with antidepressant medicines
- all treatment choices for depression or other serious mental illness

What is the most important information I should know about antidepressant medicines, depression and other serious mental illnesses, and suicidal thoughts or actions?

1.Antidepressant medicines may increase suicidal thoughts or actions in some children, teenagers, and young adults within the first few months of treatment.

2.Depression and other serious mental illnesses are the most important causes of suicidal thoughts and actions. Some people may have a particularly high risk of having suicidal thoughts or actions.These include people who have (or have a family history of) bipolar illness (also called manic-depressive illness) or suicidal thoughts or actions.

3.How can I watch for and try to prevent suicidal thoughts and actions in myself or a family member?

- Pay close attention to any changes, especially sudden changes, in mood, behaviors, thoughts, or feelings. This is very important when an antidepressant medicine is started or when the dose is changed.
- Call the healthcare provider right away to report new or sudden changes in mood, behavior, thoughts, or feelings.
- Keep all follow-up visits with the healthcare provider as scheduled. Call the healthcare provider between visits as needed, especially if you have concerns about symptoms.

Call a healthcare provider right away if you or your family member has any of the following symptoms, especially if they are new, worse, or worry you:

- thoughts about suicide or dying
- attempts to commit suicide
- new or worse depression
- new or worse anxiety
- feeling very agitated or restless
- panic attacks
- trouble sleeping (insomnia)
- new or worse irritability
- acting aggressive, being angry, or violent
- acting on dangerous impulses
- an extreme increase in activity and talking (mania)
- other unusual changes in behavior or mood
- Visual problems: eye pain, changes in vision, swelling or redness in or around the eye

What else do I need to know about antidepressant medicines?

- Never stop an antidepressant medicine without first talking to a healthcare provider.Stopping an antidepressant medicine suddenly can cause other symptoms.
- Visual problems:Only some people are at risk for these problems. You may want to undergo an eye examination to see if you are at risk and receive preventative treatment if you are.
- Antidepressants are medicines used to treat depression and other illnesses.It is important to discuss all the risks of treating depression and also the risks of not treating it. Patients and their families or other caregivers should discuss all treatment choices with the healthcare provider, not just the use of antidepressants.
- Antidepressant medicines have other side effects.Talk to the healthcare provider about the side effects of the medicine prescribed for you or your family member.
- Antidepressant medicines can interact with other medicines.Know all of the medicines that you or your family member takes. Keep a list of all medicines to show the healthcare provider. Do not start new medicines without first checking with your healthcare provider.
- Not all antidepressant medicines prescribed for children are FDA approved for use in children.Talk to your child’s healthcare provider for more information.

Call your doctor for medical advice about side effects. You may report side effects to FDA at 1-800-FDA-1088.

This Medication Guide has been approved by the U.S. Food and Drug Administration for all antidepressants.

For Medication Guide, please visit www.endo.com.

Repackaged By / Distributed By: RemedyRepack Inc.

625 Kolter Drive, Indiana, PA 15701

(724) 465-8762

PACKAGE LABEL

DRUG: Doxepin Hydrochloride

GENERIC: Doxepin Hydrochloride

DOSAGE: CAPSULE

ADMINSTRATION: ORAL

NDC: 70518-0386-0

NDC: 70518-0386-1

COLOR: white

SHAPE: CAPSULE

SCORE: No score

SIZE: 21 mm

IMPRINT: Par;222

PACKAGING: 30 in 1 BLISTER PACK

PACKAGING: 30 in 1 BLISTER PACK

ACTIVE INGREDIENT(S):

- DOXEPIN HYDROCHLORIDE 150mg in 1

INACTIVE INGREDIENT(S):

- STARCH, CORN
- D&C YELLOW NO. 10
- FD&C BLUE NO. 1
- GELATIN
- MAGNESIUM STEARATE
- SODIUM LAURYL SULFATE
- TITANIUM DIOXIDE